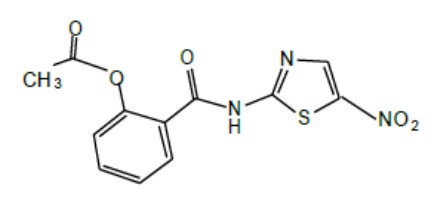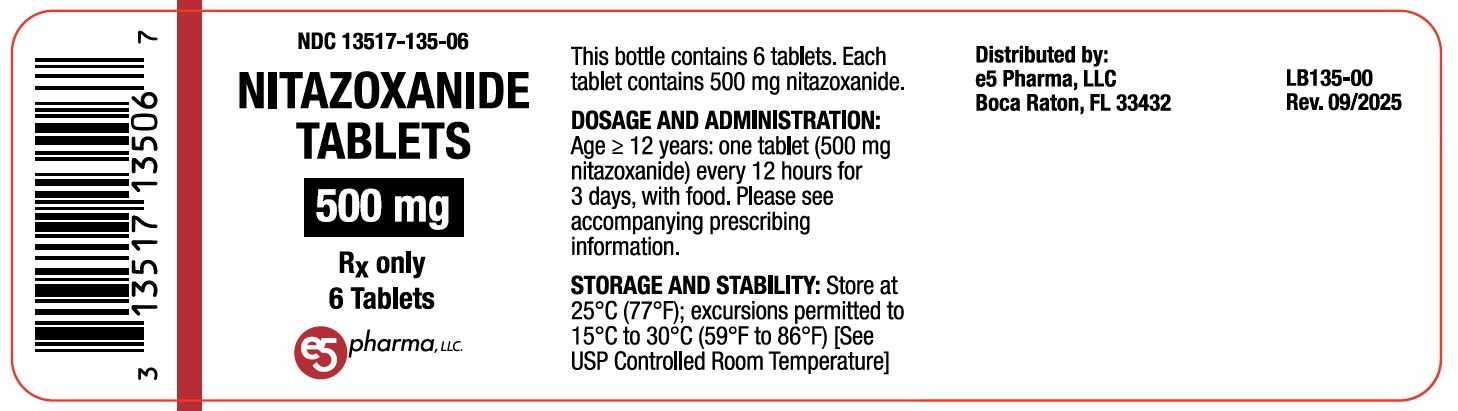 DRUG LABEL: Nitazoxanide
NDC: 13517-135 | Form: TABLET
Manufacturer: e5 Pharma, LLC
Category: prescription | Type: HUMAN PRESCRIPTION DRUG LABEL
Date: 20260122

ACTIVE INGREDIENTS: NITAZOXANIDE 500 mg/1 1
INACTIVE INGREDIENTS: STARCH, CORN; LECITHIN, SOYBEAN; XANTHAN GUM; FD&C YELLOW NO. 6 ALUMINUM LAKE; FD&C BLUE NO. 2 ALUMINUM LAKE; SUCROSE; SODIUM STARCH GLYCOLATE TYPE A; HYPROMELLOSE 2910 (50 MPA.S); TALC; MAGNESIUM STEARATE; POLYVINYL ALCOHOL; TITANIUM DIOXIDE; D&C YELLOW NO. 10 ALUMINUM LAKE

HIGHLIGHTS OF PRESCRIBING INFORMATION

These highlights do not include all the information needed to use NITAZOXANIDE TABLETS safely and effectively. See full prescribing information for NITAZOXANIDE TABLETS.
NITAZOXANIDE tablets, for oral use
Initial U.S. Approval: 2002

1 INDICATIONS & USAGE

Nitazoxanide tablet is an antiprotozoal indicated for the treatment of diarrhea caused by Giardia lamblia or Cryptosporidium parvum (1).

Limitations of Use:

Nitazoxanide tablet has not been shown to be effective for the treatment of diarrhea caused by C. parvum in HIV-infected or immunodeficient patients (1).

2 DOSAGE & ADMINISTRATION

- Nitazoxanide tablets should not be administered to pediatric patient 11 years of age or younger (2.1).
- Dosage for treatment of diarrhea caused by G. lamblia or C. parvum (2.1):

Age | Dosage | Duration
12 years and older | One nitazoxanide tablet (500 mg nitazoxanide) every 12 hours with food | 3 days

3 DOSAGE FORMS & STRENGTHS

Nitazoxanide Tablets: 500 mg (3.1)

4 CONTRAINDICATIONS

Hypersensitivity (4.1)

6 ADVERSE REACTIONS

The most common adverse reactions in ≥2% of patients were abdominal pain, headache, chromaturia, and nausea (6.1).

To report SUSPECTED ADVERSE REACTIONS, contact ANI Pharmaceuticals, Inc. at 1-855-204-1431 or FDA at 1-800-FDA-1088 or www.fda.gov/medwatch.

7 DRUG INTERACTIONS

Competition for binding sites may occur when administered concurrently with other highly plasma protein-bound drugs with narrow therapeutic indices. Monitor for adverse reactions (7).

8 USE IN SPECIFIC POPULATIONS

Pediatric Patients: Safety and efficacy of ALINIA®for Oral Suspension in pediatric patients less than one year of age has not been studied (8.4).

FULL PRESCRIBING INFORMATION

1 INDICATIONS & USAGE

Diarrhea caused by Giardia lamblia or Cryptosporidium parvum:

Nitazoxanide tablets (patients 12 years and older) are indicated for the treatment of diarrhea caused by Giardia lamblia or Cryptosporidium parvum.

Limitations of Use

Nitazoxanide tablets have not been shown to be effective for the treatment of diarrhea caused by Cryptosporidium parvum in HIV-infected or immunodeficient patients [see Clinical Studies (14.2)].

2 DOSAGE & ADMINISTRATION

2.1 Recommended Dosage and Important Administration Instructions

Important Administration Instructions for Pediatric Patients 11 years of Age or Younger:

Nitazoxanide tablets should not be administered to pediatric patients 11 years of age or younger because a single tablet contains a greater amount of nitazoxanide than the recommended dosing in this pediatric age group.

Table 1. Recommended Dosage

Age | Dosage | Duration
12 years and older | One nitazoxanide tablet (500 mg nitazoxanide) taken orally every 12 hours with food. | 3 days

3 DOSAGE FORMS & STRENGTHS

3.1 Nitazoxanide Tablets (500 mg)

Round, yellow, film-coated tablets debossed with ‘ZNN’ on one side, plain on the other side, and free from physical defects. Each tablet contains 500 mg of nitazoxanide.

4 CONTRAINDICATIONS

4.1 Hypersensitivity

Nitazoxanide tablets and ALINIA for Oral Suspension are contraindicated in patients with a prior hypersensitivity to nitazoxanide or any other ingredient in the formulations.

6 ADVERSE REACTIONS

6.1 Clinical Trials Experience

Because clinical trials are conducted under widely varying conditions, adverse reaction rates observed in the clinical trials of a drug cannot be directly compared to rates in the clinical trials of another drug and may not reflect the rates observed in practice.

The safety of nitazoxanide was evaluated in 2177 HIV-uninfected subjects 12 months of age and older who received nitazoxanide tablets or ALINIA for Oral Suspension at the recommended dose for at least three days. In pooled controlled clinical trials involving 536 HIV-uninfected subjects treated with nitazoxanide tablets or ALINIA for Oral Suspension, the most common adverse reactions were abdominal pain, headache, chromaturia and nausea (≥2%).

Safety data were analyzed separately for 280 HIV-uninfected subjects ≥12 years of age receiving nitazoxanide at the recommended dose for at least three days in 5 placebo-controlled clinical trials and for 256 HIV-uninfected subjects 1 through 11 years of age in 7 controlled clinical trials. There were no differences between the adverse reactions reported for nitazoxanide-treated subjects based upon age.

6.2 Postmarketing Experience

The following adverse reactions have been identified during post approval use of nitazoxanide. Because these reactions are reported voluntarily from a population of uncertain size, it is not always possible to reliably estimate their frequency or establish a causal relationship to drug exposure. The following is a list of adverse reactions spontaneously reported with nitazoxanide tablets which were not included in clinical trial listings:

Gastrointestinal disorders: diarrhea, gastroesophageal reflux disease

Nervous System disorders: dizziness

Respiratory, thoracic and mediastinal disorders: dyspnea

Skin and subcutaneous tissue disorders: rash, urticaria

7 DRUG INTERACTIONS

7.1 Highly Protein Bound Drugs with Narrow Therapeutic Indices

Tizoxanide (the active metabolite of nitazoxanide) is highly bound to plasma protein (>99.9%). Therefore, monitor for adverse reactions when administering nitazoxanide concurrently with other highly plasma protein-bound drugs with narrow therapeutic indices, as competition for binding sites may occur (e.g., warfarin).

8 USE IN SPECIFIC POPULATIONS

8.1 Pregnancy

Risk Summary

There are no data with nitazoxanide in pregnant women to inform a drug-associated risk. No teratogenicity or fetotoxicity was observed in animal reproduction studies with administration of nitazoxanide to pregnant rats and rabbits during organogenesis at exposures 30 and 2 times, respectively, the exposure at the maximum recommended human dose of 500 mg twice daily based on body surface area (BSA).

In the U.S. general population, the estimated background risk of major birth defects and miscarriage in clinically recognized pregnancies is 2% to 4% and 15% to 20%, respectively.

Data

Animal Data

Nitazoxanide was administered orally to pregnant rats at doses of 0, 200, 800 or 3200 mg/kg/day on gestation days 6 to 15. Nitazoxanide produced no evidence of systemic maternal toxicity when administered once daily via oral gavage to pregnant female rats at levels up to 3200 mg/kg/day during the period of organogenesis.

In rabbits, nitazoxanide was administered at doses of 0, 25, 50, or 100 mg/kg/day on gestation days 7 to 20. Oral treatment of pregnant rabbits with nitazoxanide during organogenesis resulted in minimal maternal toxicity and no external fetal anomalies.

8.2 Lactation

Risk Summary

No information regarding the presence of nitazoxanide in human milk, the effects on the breastfed infant, or the effects on milk production is available. The development and health benefits of breastfeeding should be considered along with the mother’s clinical need for nitazoxanide and any potential adverse effects on the breastfed infant from nitazoxanide or from the underlying maternal condition.

8.4 Pediatric Use

The safety and efficacy of ALINIA for Oral Suspension for the treatment of diarrhea caused by G. lamblia or C. parvum in pediatric patients 1 to 11 years of age has been established based on three (3) randomized, controlled studies with 104 pediatric subjects treated with ALINIA for Oral Suspension 100 mg/5 mL. Furthermore, the safety and efficacy of ALINIA for Oral Suspension for the treatment of diarrhea caused by G. lamblia or C. parvum in pediatric patients 12 to 17 years of age has been established based on two (2) randomized controlled studies with 44 pediatric subjects treated with ALINIA for Oral Suspension 100 mg/5 mL [see Clinical Studies (14.1)].

The safety and efficacy of nitazoxanide tablets for the treatment of diarrhea caused by G. lamblia or C. parvum in pediatric patients 12 to 17 years of age has been established based on three (3) randomized controlled studies with 47 pediatric subjects treated with nitazoxanide tablets 500 mg.

A single nitazoxanide tablet contains a greater amount of nitazoxanide than is recommended for use in pediatric patients 11 years or younger. [see Dosage and Administration (2.1)].

Safety and efficacy of ALINIA for Oral Suspension in pediatric patients less than one year of age has not been studied.

8.5 Geriatric Use

Clinical studies of nitazoxanide tablets and ALINIA for Oral Suspension did not include sufficient numbers of subjects aged 65 and over to determine whether they respond differently from younger subjects. In general, the greater frequency of decreased hepatic, renal, or cardiac function, and of concomitant disease or other drug therapy in elderly patients should be considered when prescribing nitazoxanide tablets and ALINIA for Oral Suspension.

8.6 Renal and Hepatic Impairment

The pharmacokinetics of nitazoxanide in patients with compromised renal or hepatic function has not been studied.

8.7 HIV-Infected or Immunodeficient Patients

Nitazoxanide tablets and ALINIA for Oral Suspension have not been studied for the treatment of diarrhea caused by G. lamblia in HIV-infected or immunodeficient patients. Nitazoxanide tablets and ALINIA for Oral Suspension have not been shown to be superior to placebo for the treatment of diarrhea caused by C. parvum in HIV-infected or immunodeficient patients [see Clinical Studies (14)].

10 OVERDOSAGE

Limited information on nitazoxanide overdosage is available. In the event of overdose, gastric lavage may be appropriate soon after oral administration. Patients should be observed and given symptomatic and supportive treatment. There is no specific antidote for overdose with nitazoxanide. Because tizoxanide is highly protein bound (>99.9%), dialysis is unlikely to significantly reduce plasma concentrations of the drug.

11 DESCRIPTION

Nitazoxanide tablets contain the active ingredient, nitazoxanide, a synthetic antiprotozoal for oral administration. Nitazoxanide is a light yellow crystalline powder. It is poorly soluble in ethanol and practically insoluble in water. Chemically, nitazoxanide is 2-acetyloxy-N-(5-nitro-2-thiazolyl)benzamide. The molecular formula is C12H9N3O5S and the molecular weight is 307.3. The structural formula is:

Nitazoxanide tablets contain 500 mg of nitazoxanide and the following inactive ingredients: corn starch, sodium starch glycolate type A, sucrose, hydroxypropyl methylcellulose, talc, magnesium stearate, polyvinyl alcohol, titanium dioxide, D&C yellow #10 aluminum lake, lecithin (soy), xanthan gum, FD&C yellow #6 aluminum lake, FD&C blue #2 aluminum lake.

12 CLINICAL PHARMACOLOGY

12.1 Mechanism of Action

Nitazoxanide is an antiprotozoal [see Microbiology (12.4)].

12.3 Pharmacokinetics

Absorption

Single Dosing:

Following oral administration of nitazoxanide tablets or ALINIA for Oral Suspension, the parent drug, nitazoxanide, is not detected in plasma. The pharmacokinetic parameters of the metabolites, tizoxanide and tizoxanide glucuronide are shown in Tables 2 and 3 below.

Table 2. Mean (±SD) plasma pharmacokinetic parameters of tizoxanide and tizoxanide glucuronide following administration of a single dose of one 500 mg nitazoxanide tablet with food to subjects ≥12 years of age

 | Tizoxanide |  |  | Tizoxanide Glucuronide
Age | Cmax | *Tmax | AUCτ | Cmax | *Tmax | AUCτ
Age | (µg/mL) | (hr) | (µg•hr/mL) | (µg/mL) | (hr) | (µg•hr/mL)
12-17 years | 9.1 (6.1) | 4.0 (1-4) | 39.5 (24.2) | 7.3 (1.9) | 4.0 (2-8) | 46.5 (18.2)
≥18 years | 10.6 (2.0) | 3.0 (2-4) | 41.9 (6.0) | 10.5 (1.4) | 4.5 (4-6) | 63.0 (12.3)

* Tmax is given as a Mean (Range)

Table 3. Mean (±SD) plasma pharmacokinetic of tizoxanide and tizoxanide glucuronide parameter values following administration of a single dose of ALINIA for Oral Suspension with food to subjects ≥1 year of age

 |  | Tizoxanide |  |  | Tizoxanide Glucuronide
Age | Dose | Cmax | *Tmax | AUCinf | Cmax | *Tmax | AUCinf
Age | Dose | (µg/mL) | (hr) | (µg•hr/mL) | (µg/mL) | (hr) | (µg•hr/mL)
1-3 years | 100 mg | 3.11 (2.0) | 3.5 (2-4) | 11.7 (4.46) | 3.64 (1.16) | 4.0 (3-4) | 19.0 (5.03)
4-11 years | 200 mg | 3.00 (0.99) | 2.0 (1-4) | 13.5 (3.3) | 2.84 (0.97) | 4.0 (2-4) | 16.9 (5.00)
≥18 years | 500 mg | 5.49 (2.06) | 2.5 (1-5) | 30.2 (12.3) | 3.21 (1.05) | 4.0 (2.5-6) | 22.8 (6.49)

* Tmax is given as a Mean (Range)

Multiple dosing:

Following oral administration of a single nitazoxanide tablet every 12 hours for 7 consecutive days, there was no significant accumulation of nitazoxanide metabolites tizoxanide or tizoxanide glucuronide detected in plasma.

Bioavailability:

ALINIA for Oral Suspension is not bioequivalent to nitazoxanide tablets. The relative bioavailability of the suspension compared to the tablet was 70%.

When nitazoxanide tablets are administered with food, the AUCτ of tizoxanide and tizoxanide glucuronide in plasma is increased almost two-fold and the Cmax is increased by almost 50%.

When ALINIA for Oral Suspension was administered with food, the AUCτ of tizoxanide and tizoxanide glucuronide increased by about 45-50% and the Cmax increased by ≤10%.

Nitazoxanide tablets and ALINIA for Oral Suspension were administered with food in clinical trials and hence they are recommended to be administered with food [see Dosage and Administration (2.1)].

Distribution

In plasma, more than 99% of tizoxanide is bound to proteins.

Elimination

Metabolism

Following oral administration in humans, nitazoxanide is rapidly hydrolyzed to an active metabolite, tizoxanide (desacetyl-nitazoxanide). Tizoxanide then undergoes conjugation, primarily by glucuronidation.

Excretion

Tizoxanide is excreted in the urine, bile and feces, and tizoxanide glucuronide is excreted in urine and bile. Approximately two-thirds of the oral dose of nitazoxanide is excreted in the feces and one-third in the urine.

Specific Populations

Pediatric Patients

The pharmacokinetics of tizoxanide and tizoxanide glucuronide following administration of nitazoxanide tablets in pediatric patients 12-17 years of age are provided above in Table 2. Mean (±SD) plasma pharmacokinetic parameters of tizoxanide and tizoxanide glucuronide following administration of a single dose of one 500 mg nitazoxanide tablet with food to subject ≥12 years of age. The pharmacokinetics of tizoxanide and tizoxanide glucuronide following administration of ALINIA for Oral Suspension in pediatric patients 1-11 years of age are provided above in Table 3. Mean (±SD) plasma pharmacokinetic of tizoxanide and tizoxanide glucuronide parameter values following administration of a single dose of ALINIA for Oral suspension with food to subjects ≥1 year of age.

Drug Interaction Studies

In vitro studies demonstrated that tizoxanide has no significant inhibitory effect on cytochrome P450 enzymes.

12.4 Microbiology

Mechanism of Action

The antiprotozoal activity of nitazoxanide is believed to be due to interference with the pyruvate:ferredoxin oxidoreductase (PFOR) enzyme-dependent electron transfer reaction which is essential to anaerobic energy metabolism. Studies have shown that the PFOR enzyme from G. lamblia directly reduces nitazoxanide by transfer of electrons in the absence of ferredoxin. The DNA-derived PFOR protein sequence of C. parvum appears to be similar to that of G. lamblia. Interference with the PFOR enzyme-dependent electron transfer reaction may not be the only pathway by which nitazoxanide exhibits antiprotozoal activity.

Resistance

A potential for development of resistance by C. parvum or G. lamblia to nitazoxanide has not been examined.

Antimicrobial Activity

Nitazoxanide and its metabolite, tizoxanide, are active in vitro in inhibiting the growth of (i) sporozoites and oocysts of C. parvum and (ii) trophozoites of G. lamblia.

Susceptibility Test Methods

For protozoa such as C. parvum and G. lamblia, standardized tests for use in clinical microbiology laboratories are not available.

13 NONCLINICAL TOXICOLOGY

13.1 Carcinogenesis & Mutagenesis & Impairment Of Fertility

Carcinogenesis

Long-term carcinogenicity studies have not been conducted.

Mutagenesis

Nitazoxanide was not genotoxic in the Chinese hamster ovary (CHO) cell chromosomal aberration assay or the mouse micronucleus assay. Nitazoxanide was genotoxic in one tester strain (TA 100) in the Ames bacterial mutation assay.

Impairment of Fertility

Nitazoxanide did not adversely affect male or female fertility in the rat at 2400 mg/kg/day (approximately 20 times the clinical adult dose adjusted for body surface area).

14 CLINICAL STUDIES

14.1 Diarrhea Caused by G. lamblia

Diarrhea caused by G. lamblia in adults and adolescents 12 years of age or older:

In a double-blind, controlled trial (Study 1) conducted in Peru and Egypt in adults and adolescents with diarrhea and with one or more enteric symptoms (e.g., abdominal pain, nausea, vomiting, fever, abdominal distention, loss of appetite, flatulence) caused by G. lamblia, a three-day course of treatment with nitazoxanide tablets administered 500 mg twice daily was compared with a placebo tablet for 3 days. A third group of patients received open-label ALINIA for Oral Suspension administered 500 mg/25mL of suspension twice daily for 3 days. A second double-blind, controlled trial (Study 2) conducted in Egypt in adults and adolescents with diarrhea and with or without enteric symptoms (e.g., abdominal colic, abdominal tenderness, abdominal cramps, abdominal distention, fever, bloody stool) caused by G. lamblia compared nitazoxanide tablets administered 500 mg twice daily for 3 days to a placebo tablet. For both of these studies, clinical response was evaluated 4 to 7 days following the end of treatment. A clinical response of ‘well’ was defined as ‘no symptoms, no watery stools and no more than 2 soft stools with no hematochezia within the past 24 hours’ or ‘no symptoms and no unformed stools within the past 48 hours.’ The following clinical response rates were obtained:

Table 4. Adult and Adolescent Patients with Diarrhea Caused by G. lamblia Clinical Response Rates* 4 to 7 Days Post-therapy % (Number of Successes/Total)

 | Nitazoxanide Tablets | ALINIA for Oral Suspension | Placebo Tablets
Study 1 | 85% (46/54)¶ § | 83% (45/54)¶ § | 44% (12/27)
Study 2 | 100% (8/8) | - | 30% (3/10)

*Includes all patients randomized with G. lamblia as the sole pathogen. Patients failing to complete the studies were treated as failures.

¶Clinical response rates statistically significantly higher when compared to placebo.

§The 95% confidence interval of the difference in response rates for the tablet and suspension is (-14%, 17%).

Some patients with ‘well’ clinical responses had G. lamblia cysts in their stool samples 4 to 7 days following the end of treatment. The relevance of stool examination results in these patients is unknown. Patients should be managed based upon clinical response to treatment.

Diarrhea caused by G. lamblia in pediatric patients 1 through 11 years of age:

In a randomized, controlled trial conducted in Peru in 110 pediatric patients with diarrhea and with or without enteric symptoms (e.g., abdominal distention, right iliac fossa tenderness) caused by G. lamblia, a three-day course of treatment with nitazoxanide (100 mg twice daily in pediatric patients ages 24-47 months, 200 mg twice daily in pediatric patients ages 4 through 11 years) was compared to a five-day course of treatment with metronidazole (125 mg twice daily in pediatric patients ages 2 through 5 years, 250 mg twice daily in pediatric patients ages 6 through 11 years). Clinical response was evaluated 7 to 10 days following initiation of treatment with a ‘well’ response defined as ‘no symptoms, no watery stools and no more than 2 soft stools with no hematochezia within the past 24 hours’ or ‘no symptoms and no unformed stools within the past 48 hours.’ The following clinical response rates were obtained:

Table 5. Clinical Response Rates in Pediatric Patients 7 to 10 Days Following Initiation of Therapy Intent-to-Treat and Per Protocol Analyses % (Number of Successes/Total), [95% Confidence Interval]

Population | Nitazoxanide (3 days) | Metronidazole (5 days) | 95% CI Diff§
Intent-to-treat analysis† | 85% (47/55) | 80% (44/55) | [-9%, 20%]
Per protocol analysis¶ | 90% (43/48) | 83% (39/47) | [-8%, 21%]

†Intent-to-treat analysis includes all patients randomized with patients not completing the study treated as failures.

¶Per protocol analysis includes only patients who took all of their medication and completed the study. Seven patients in each treatment group missed at least one dose of medication and one in the metronidazole treatment group was lost to follow-up.

§95% Confidence Interval on the difference in response rates (nitazoxanide-metronidazole).

Some patients with ‘well’ clinical responses had G. lamblia cysts in their stool samples 4 to 7 days following the end of treatment. The relevance of stool examination results in these patients is unknown. Patients should be managed based upon clinical response to treatment.

14.2 Diarrhea Caused by C. parvum

Diarrhea caused by C. parvum in adults and adolescents 12 years of age or older:

In a double-blind, controlled trial conducted in Egypt in adults and adolescents with diarrhea and with or without enteric symptoms (e.g., abdominal pain/cramps, nausea, vomiting) caused by C. parvum, a three-day course of treatment with nitazoxanide tablets administered 500 mg twice daily was compared with a placebo tablet for 3 days. A third group of patients received open-label ALINIA for Oral Suspension administered 500 mg/25 mL of suspension twice daily for 3 days. Clinical response was evaluated 4 to 7 days following the end of treatment. A clinical response of ‘well’ was defined as ‘no symptoms, no watery stools and no more than 2 soft stools within the past 24 hours’ or ‘no symptoms and no unformed stools within the past 48 hours.’ The following clinical response rates were obtained:

Table 6. Clinical Response Rates in Adult and Adolescent Patients 4 to 7 Days Post-therapy% (Number of Successes/Total)

 | Nitazoxanide Tablets | ALINIA for Oral Suspension | Placebo Tablets
Intent-to-treat analysis* | 96% (27/28) ¶ § | 87% (27/31) ¶ § | 41% (11/27)

*Includes all patients randomized with C. parvum as the sole pathogen. Patients failing to complete the study were treated as failures.

¶Clinical response rates statistically significantly higher when compared to placebo.

§The 95% confidence interval of the difference in response rates for the tablet and suspension is (-10%, 28%).

In a second double-blind, placebo-controlled trial of nitazoxanide tablets conducted in Egypt in adults and adolescents with diarrhea and with or without enteric symptoms (e.g., abdominal colic, abdominal cramps, epigastric pain) caused by C. parvum as the sole pathogen, clinical and parasitological response rates showed a similar trend to the first study. Clinical response rates, evaluated 2 to 6 days following the end of treatment, were 71% (15/21) in the nitazoxanide group and 42.9% (9/21) in the placebo group.

Some patients with ‘well’ clinical responses had C. parvum oocysts in their stool samples 4 to 7 days following the end of treatment. The relevance of stool examination results in these patients is unknown. Patients should be managed based upon clinical response to treatment.

Diarrhea caused by C. parvum in pediatric patients 1 through 11 years of age:

In two double-blind, controlled trials in pediatric patients with diarrhea and with or without enteric symptoms (e.g., abdominal distention, colic, left iliac fossa tenderness) caused by C. parvum, a three-day course of treatment with nitazoxanide (100 mg twice daily in pediatric patients ages 12-47 months, 200 mg twice daily in pediatric patients ages 4 through 11 years) was compared with a placebo. One study was conducted in Egypt in outpatients ages 1 through 11 years with diarrhea caused by C. parvum. Another study was conducted in Zambia in malnourished pediatric patients admitted to the hospital with diarrhea caused by C. parvum. Clinical response was evaluated 3 to 7 days post-therapy with a ‘well’ response defined as ‘no symptoms, no watery stools and no more than 2 soft stools within the past 24 hours’ or ‘no symptoms and no unformed stools within the past 48 hours.’ The following clinical response rates were obtained:

Table 7. Clinical Response Rates in Pediatric Patients 3 to 7 Days Post-therapy Intent-to-Treat Analyses % (Number of Successes/Total)

Population | Nitazoxanide* | Placebo
Outpatient Study, age 1 - 11 years | 88% (21/24) | 38% (9/24)
Inpatient Study, Malnourished¶, age 12-35 months | 56% (14/25) | 23% (5/22)

*Clinical response rates statistically significantly higher compared to placebo.

¶ 60% considered severely underweight, 19% moderately underweight, 17% mild underweight.

Some patients with ‘well’ clinical responses had C. parvum oocysts in their stool samples 3 to 7 days following the end of treatment. The relevance of stool examination results in these patients is unknown. Patients should be managed based upon clinical response to treatment.

Diarrhea caused by C. parvum in Acquired Immune Deficiency Syndrome (AIDS) patients:

A double-blind, placebo-controlled trial did not produce clinical cure rates that were significantly different from the placebo control when conducted in hospitalized, severely malnourished pediatric patients with acquired immune deficiency syndrome (AIDS) in Zambia. In this study, the pediatric patients received a three day course of nitazoxanide suspension (100 mg twice daily in pediatric patients ages 12-47 months, 200 mg twice daily in pediatric patients ages 4 through 11 years) and were evaluated for response four days after the end of treatment.

16 HOW SUPPLIED/STORAGE AND HANDLING

16.1 Nitazoxanide Tablets (500 mg)

Nitazoxanide Tablets are round, yellow, film-coated tablets debossed with ‘ZNN’ on one side, plain on the other side, and free from physical defects. Each tablet contains 500 mg of nitazoxanide. The tablets are packaged in HDPE bottles as:

Bottles of 6 tablets NDC 13517-135-06

Store the tablets at 25°C (77°F); excursions permitted to 15°C to 30°C (59°F to 86°F) [See USP Controlled Room Temperature].

17 PATIENT COUNSELING INFORMATION

Advise patients and parents/caregivers of pediatric patients taking nitazoxanide tablets of the following information:

Dosage and Administration:

Nitazoxanide tablets should be taken with food.

Drug-drug Interactions:

Avoid concurrent warfarin use.

All trademarks are the property of their respective owners.

Distributed by:
e5 Pharma, LLC
Boca Raton, FL 33432

Rev. 09/2025
IN135-00

PACKAGE LABEL.PRINCIPAL DISPLAY PANEL

Nitazoxanide Tablets, 500 mg

Bottles of 6 tablets NDC 13517-135-06